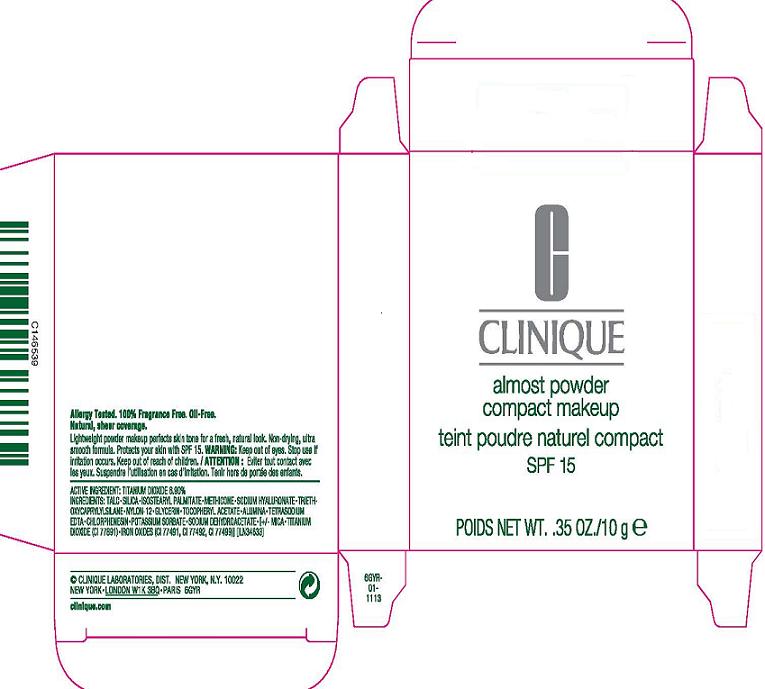 DRUG LABEL: ALMOST POWDER
NDC: 49527-724 | Form: POWDER
Manufacturer: CLINIQUE LABORATORIES INC
Category: otc | Type: HUMAN OTC DRUG LABEL
Date: 20110803

ACTIVE INGREDIENTS: TITANIUM DIOXIDE 6.9 g/100 g
INACTIVE INGREDIENTS: TALC; SILICON DIOXIDE; DIMETHICONE; HYALURONATE SODIUM; TRIETHOXYCAPRYLYLSILANE; GLYCERIN; ALPHA-TOCOPHEROL ACETATE; ALUMINUM OXIDE; EDETATE SODIUM; CHLORPHENESIN; POTASSIUM SORBATE; SODIUM DEHYDROACETATE; FERRIC OXIDE RED; MICA

ACTIVE INGREDIENT: TITANIUM DIXOIDE, 6.9%

INACTIVE INGREDIENT

INACTIVE INGREDIENTS: talc [] silica [] isostearyl palmitate [] methicone [] sodium hyaluronate [] triethoxycaprylylsilane [] nylon-12 [] glycerin [] tocopheryl acetate [] alumina [] tetrasodium edta [] chlorphenesin [] potassium sorbate [] sodium dehydroacetate [] [+/- mica [] titanium dioxide (ci 77891) [] iron oxides (ci 77491, ci 77492, ci 77499)]

WARNINGS

WARNING: KEEP OUT OF EYES. STOP USE IF IRRITATION OCCURS. KEEP OUT OF REACH OF CHILDREN.

PACKAGE LABEL

PRINCIPAL DISPLAY PANEL:

CLINIQUE

ALMOST POWDER

COMPACT MAKEUP

SPF 15

NT WT..35 OZ / 10 g

CLINIQUE LABORATORIES, DIST

NY, NY 10022